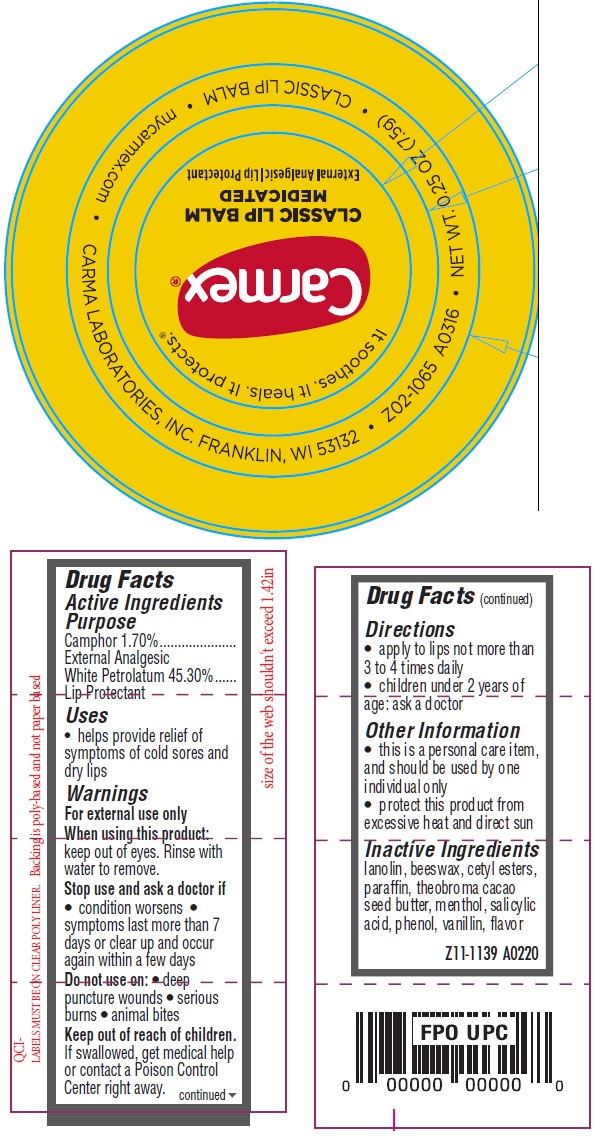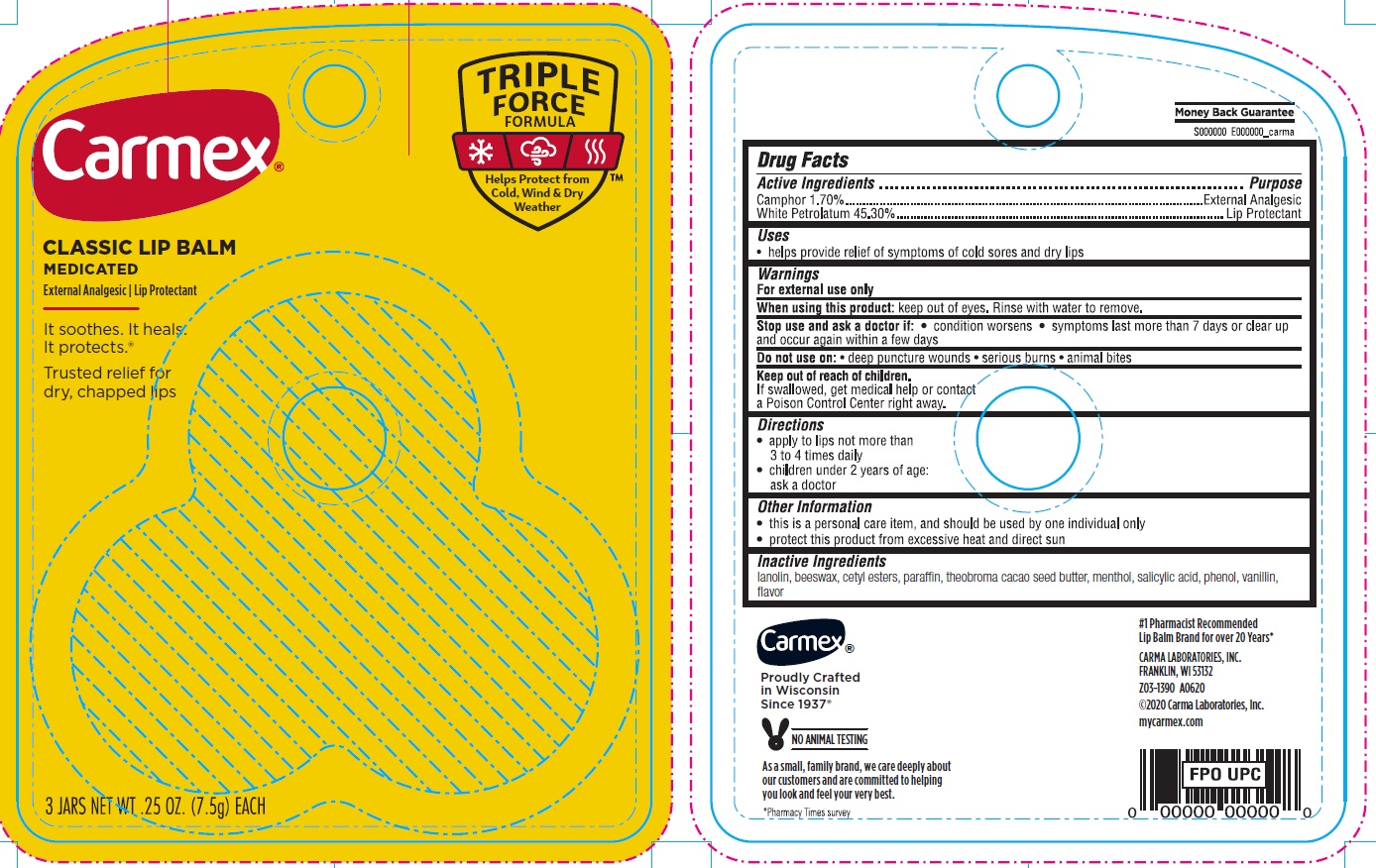 DRUG LABEL: Carmex Classic Lip Balm Medicated
NDC: 10210-0039 | Form: SALVE
Manufacturer: Carma Laboratories, Inc.
Category: otc | Type: HUMAN OTC DRUG LABEL
Date: 20231025

ACTIVE INGREDIENTS: CAMPHOR (SYNTHETIC) 17 mg/1 g; WHITE PETROLATUM 453 mg/1 g
INACTIVE INGREDIENTS: LANOLIN; YELLOW WAX; CETYL ESTERS WAX; PARAFFIN; MENTHOL; SALICYLIC ACID; PHENOL; VANILLIN

Carmex Classic Lip Balm Medicated

Active Ingredients

Camphor 1.70%

White Petrolatum 45.30%

Purpose

External Analgesic

Lip Protectant

Uses

• helps provide relief of symptoms of cold sores and dry lips

Warnings

For external use only

When using this product:

keep out of eyes. Rinse with water to remove.

Stop use and ask a doctor if

• condition worsens • symptoms last more than 7 days or clear up and occur again within a few days

Do not use on:

• deep puncture wounds • serious burns • animal bites

Keep out of reach of children.

If swallowed, get medical help or contact a Poison Control Center right away.

Directions

• apply to lips not more than 3 to 4 times daily • children under 2 years of age: ask a doctor

Other Information

• this is a personal care item, and should be used by one individual only • protect this product from excessive heat and direct sun

Inactive Ingredients

lanolin, beeswax, cetyl esters, paraffin, theobroma cacao seed butter, menthol, salicylic acid, phenol, vanillin, flavor